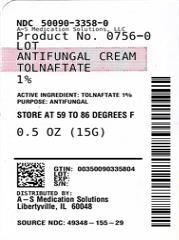 DRUG LABEL: sunmark 
NDC: 50090-3358 | Form: CREAM
Manufacturer: A-S Medication Solutions
Category: otc | Type: HUMAN OTC DRUG LABEL
Date: 20231216

ACTIVE INGREDIENTS: TOLNAFTATE 10 mg/1 g
INACTIVE INGREDIENTS: Butylated Hydroxytoluene; Polyethylene Glycol 400; Polyethylene Glycol 3350; titanium dioxide; petrolatum

sunmark™
antifungal

Drug Facts

Active ingredient

Tolnaftate 1%

Purpose

Antifungal

Uses

- clinically proven to cure most athlete's foot (tinea pedis), jock itch (tinea cruris) and ringworm (tinea corporis)
- helps prevent most athlete's foot from recurring when used daily
- effectively soothes and relieves symptoms of athlete's foot, including itching, burning and cracking

Warnings

For external use only

When using this product avoid contact with the eyes

Stop use and ask a doctor if

- irritation occurs
- there is no improvement within 4 weeks (for athlete's foot or ringworm) or within 2 weeks (for jock itch)

Do not use on children under 2 years of age except under the advice and supervision of a doctor.

Keep out of reach of children. If swallowed, get medical help or contact a Poison Control Center right away.

Directions

- wash affected area and dry thoroughly
- apply a thin layer over affected area twice daily (morning and night)
- supervise children in the use of this product
- this product is not effective on scalp or nails

For athlete's foot

- pay special attention to spaces between toes
- wear well-fitting shoes, change shoes and socks at least once daily

For athlete's foot and ringworm use daily for 4 weeks

For jock itch use daily for 2 weeks
If condition persists longer, consult a doctor

Other information

- Store between 15° - 30°C (59° - 86°F)
- See end panel of carton and tube crimp for lot number and expiration date

Inactive ingredients

BHT, PEG-400, PEG-3350, titanium dioxide, white petrolatum

Distributed by McKesson
One Post Street
San Francisco, CA 94104

HOW SUPPLIED

Product: 50090-3358

NDC: 50090-3358-0 15 g in a TUBE / 1 in a CARTON